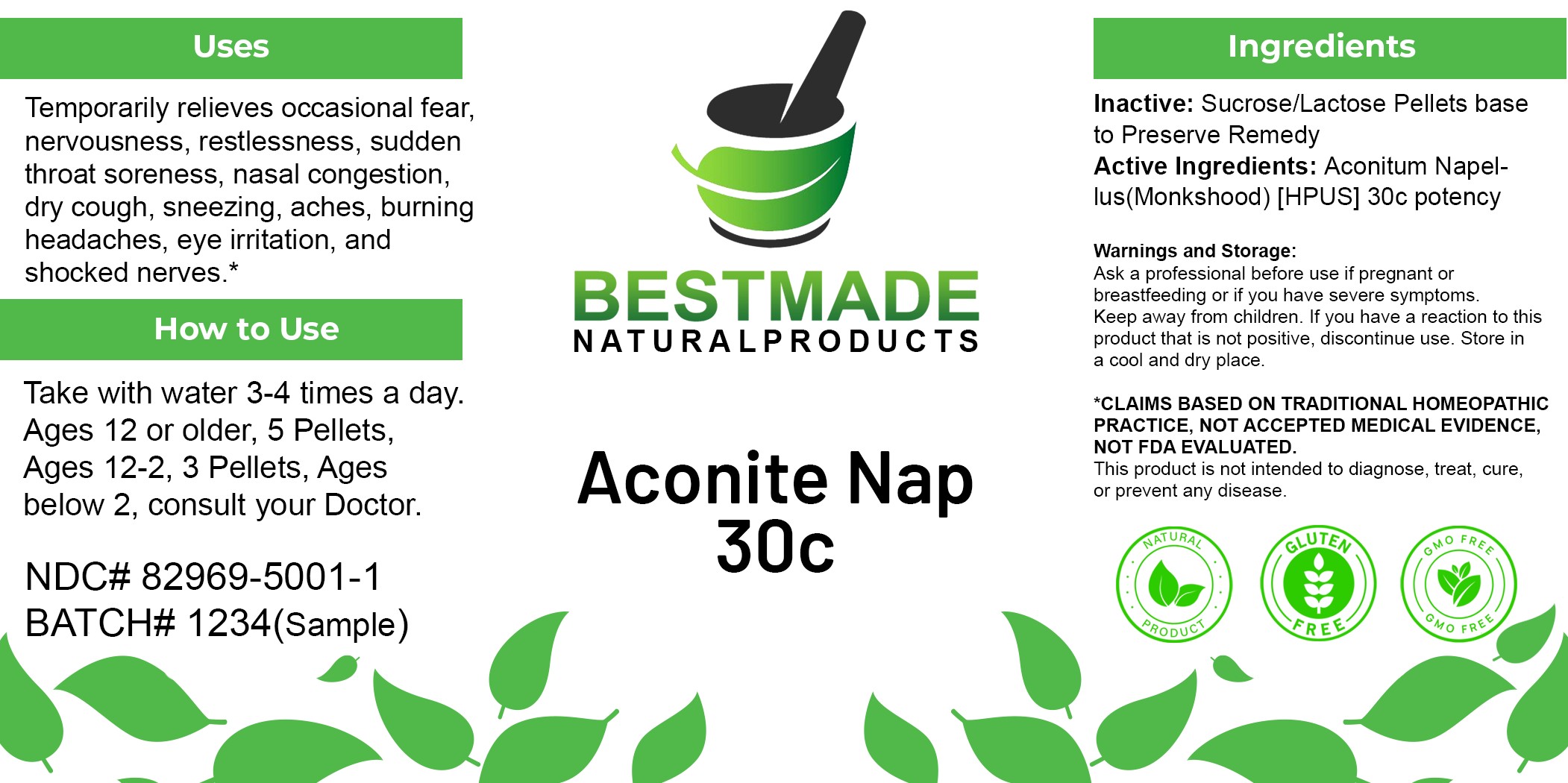 DRUG LABEL: Bestmade Natural Products Aconitum Napellus
NDC: 82969-5001 | Form: TABLET, SOLUBLE
Manufacturer: Bestmade Natural Products
Category: homeopathic | Type: HUMAN OTC DRUG LABEL
Date: 20250527

ACTIVE INGREDIENTS: ACONITUM NAPELLUS 30 [hp_C]/30 [hp_C]
INACTIVE INGREDIENTS: LACTOSE 30 [hp_C]/30 [hp_C]; SUCROSE 30 [hp_C]/30 [hp_C]

ACONITUM NAPELLUS 30C

DOSAGE AND ADMINISTRATION

How to Use

Take with water 3-4 times a day. Ages 12 or older, 5 Pellets, Ages 12-2, 3 Pellets, Ages below 2, consult your Doctor.

INDICATIONS AND USAGE

Temporarily relieves occasional fear, nervousness, restlessness, sudden throat soreness, nasal congestion, dry cough, sneezing, aches, burning headaches, eye irritation, and shocked nerves.*

INACTIVE INGREDIENT

Ingredients

Inactive: Sucrose/Lactose Pellets base to Preserve Remedy

Active Ingredients: Aconitum Napellus (Monkshood) [HPUS] 30c potency

KEEP OUT OF REACH OF CHILDREN

Warnings and Storage:
Ask a professional before use if pregnant or breastfeeding or if you have severe symptoms.
Keep away from children.
If you have a reaction to this product that is not positive, discontinue use.
Store in a cool and dry place.
*CLAIMS BASED ON TRADITIONAL HOMEOPATHIC PRACTICE, NOT ACCEPTED MEDICAL EVIDENCE, NOT FDA EVALUATED.
This product is not intended to diagnose, treat, cure, or prevent any disease.

PURPOSE

Temporarily relieves occasional fear, nervousness, restlessness, sudden throat soreness, nasal congestion, dry cough, sneezing, aches, burning headaches, eye irritation, and shocked nerves.*

Warnings and Storage:
Ask a professional before use if pregnant or breastfeeding or if you have severe symptoms.
Keep away from children.
If you have a reaction to this product that is not positive, discontinue use.
Store in a cool and dry place.
*CLAIMS BASED ON TRADITIONAL HOMEOPATHIC PRACTICE, NOT ACCEPTED MEDICAL EVIDENCE, NOT FDA EVALUATED.
This product is not intended to diagnose, treat, cure, or prevent any disease.

Entire package label